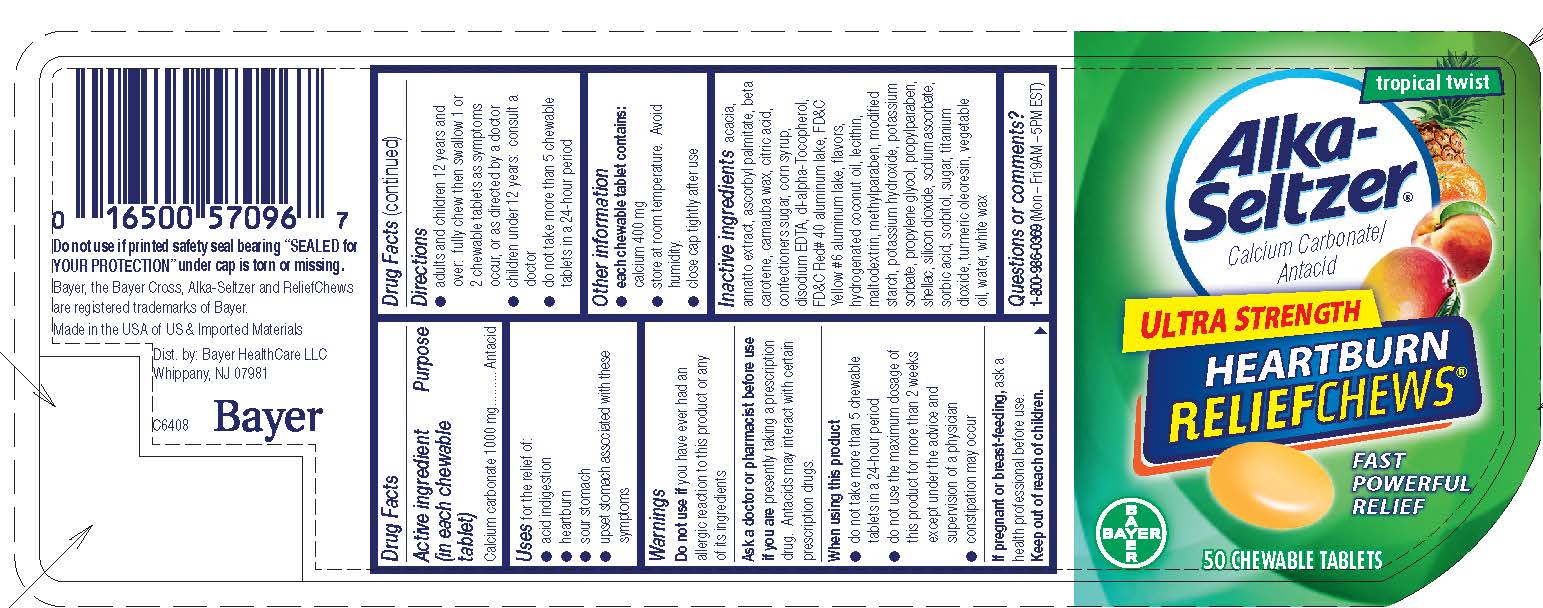 DRUG LABEL: Alka-Seltzer Ultra Strength Heartburn ReliefChews
NDC: 0280-0245 | Form: TABLET, CHEWABLE
Manufacturer: Bayer HealthCare LLC.
Category: otc | Type: HUMAN OTC DRUG LABEL
Date: 20251204

ACTIVE INGREDIENTS: CALCIUM CARBONATE 1000 mg/1 1
INACTIVE INGREDIENTS: SHELLAC; POTASSIUM SORBATE; TITANIUM DIOXIDE; TURMERIC; ANNATTO; .ALPHA.-TOCOPHEROL, DL-; MALTODEXTRIN; SODIUM ASCORBATE; WATER; PROPYLPARABEN; ASCORBYL PALMITATE; SUNFLOWER OIL; STARCH, POTATO; COCONUT OIL; CORN OIL; PALM OIL; SILICON DIOXIDE; SORBIC ACID; SORBITOL; ACACIA; CITRIC ACID MONOHYDRATE; EDETATE DISODIUM; HYDROGENATED COCONUT OIL; WHITE WAX; CARNAUBA WAX; .BETA.-CAROTENE; FD&C RED NO. 40; FD&C YELLOW NO. 6; POTASSIUM HYDROXIDE; CORN SYRUP; METHYLPARABEN; LECITHIN, SOYBEAN; PROPYLENE GLYCOL; SUCROSE

Alka-Seltzer Ultra Strength Heartburn ReliefChews UI

Drug Facts

Active ingredient (in each chewable tablet)

Calcium carbonate 1000 mg

Purpose

Antacid

Uses

Uses for the relief of:

● acid indigestion ● heartburn ● sour stomach

● upset stomach associated with these symptoms

Warnings

Do not use if you have ever had an allergic reaction to this product or any of its ingredients

Ask a doctor or pharmacist before use if you are presently taking a prescription drug. Antacids may interact with certain prescription drugs.

When using this product
● do not take more than 5 chewable tablets in a 24-hour period

● do not use the maximum dosage of this product for more than 2 weeks except under the advice and supervision of a physician

● constipation may occur

PREGNANCY OR BREAST FEEDING

If pregnant or breast-feeding, ask a health professional before use.

Keep out of reach of children

Directions

● adults and children 12 years and over: fully chew then swallow 1 or 2 chewable tablets as symptoms occur, or as directed by a doctor

● children under 12 years: consult a doctor

● do not take more than 5 chewable tablets in a 24-hour period

Other

Other information

● each chewable tablet contains: calcium 400 mg

● store at room temperature. Avoid humidity.

● close cap tightly after use

INACTIVE INGREDIENT

Inactive ingredients acacia, annatto extract, ascorbyl palmitate, beta carotene, carnauba wax, citric acid, confectioners sugar, corn syrup, disodium EDTA, dl-alpha-Tocopherol, FD&C Red #40 aluminum lake, FD&C Yellow #6 aluminum lake, flavors, hydrogenated coconut oil, lecithin, maltodextrin, methylparaben, modified starch, potassium hydroxide, potassium sorbate, propylene glycol, propylparaben, shellac, silicon dioxide, sodium ascorbate, sorbic acid, sorbitol, sugar, titanium dioxide, turmeric oleoresin, vegetable oil, water, white wax

Questions or comments?

1-800-986-0369 (Mon – Fri 9AM – 5PM EST)

Package label 50 count

tropical twist

Alka-Seltzer®

Calcium Carbonate/Antacid

ULTRA STRENGTH

HEARTBURN

RELIEFCHEWS®

FAST POWERFUL RELIEF

50 CHEWABLE TABLETS